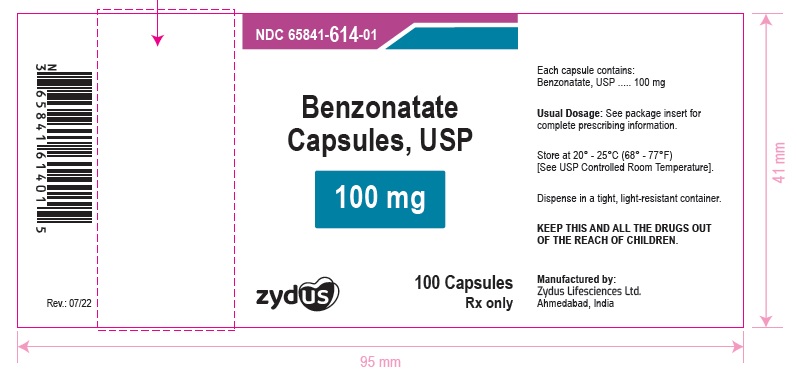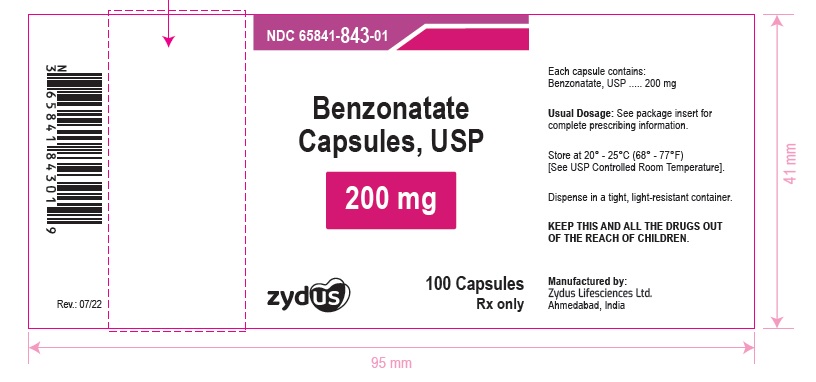 DRUG LABEL: Benzonatate
NDC: 65841-614 | Form: CAPSULE
Manufacturer: Zydus Lifesciences Limited
Category: prescription | Type: HUMAN PRESCRIPTION DRUG LABEL
Date: 20241125

ACTIVE INGREDIENTS: BENZONATATE 100 mg/1 1
INACTIVE INGREDIENTS: GLYCERIN; METHYLPARABEN; PROPYLPARABEN; SORBITOL; WATER; GELATIN

Benzonatate Capsules, USP

PACKAGE LABEL.PRINCIPAL DISPLAY PANEL

NDC 65841-614-01 in bottle of 100 capsules

Benzonatate Capsules USP, 100 mg

Rx only

100 capsules

NDC 65841-843-01 in bottle of 100 capsules

Benzonatate Capsules USP, 200 mg

Rx only

100 capsules